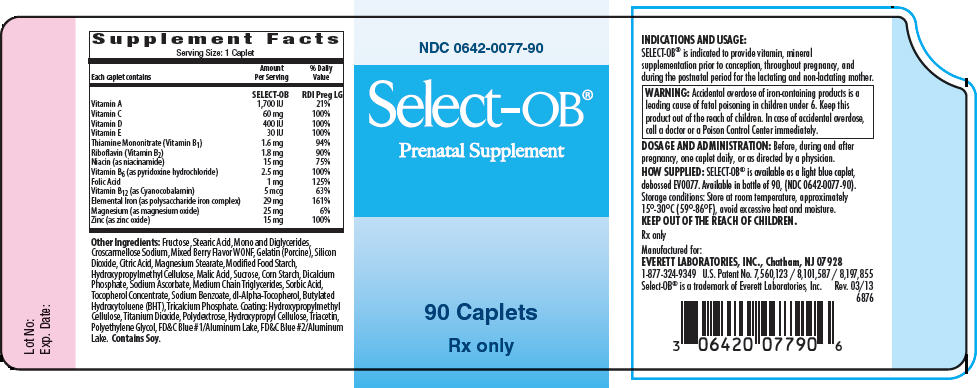 DRUG LABEL: Select OB
NDC: 0642-0077 | Form: TABLET, CHEWABLE
Manufacturer: Everett Laboratories, Inc.
Category: prescription | Type: HUMAN PRESCRIPTION DRUG LABEL
Date: 20140922

ACTIVE INGREDIENTS: .Beta.-Carotene 600 [iU]/1 1; VITAMIN A ACETATE 1100 [iU]/1 1; Ascorbic Acid 60 mg/1 1; CHOLECALCIFEROL 400 [iU]/1 1; .ALPHA.-TOCOPHEROL ACETATE, DL- 30 [iU]/1 1; THIAMINE MONONITRATE 1.6 mg/1 1; Riboflavin 1.8 mg/1 1; Niacin 15 mg/1 1; Pyridoxine Hydrochloride 2.5 mg/1 1; Folic Acid 0.4 mg/1 1; LEVOMEFOLATE CALCIUM 0.6 mg/1 1; Cobalamin 5 ug/1 1; Iron 29 mg/1 1; Magnesium 25 mg/1 1; Zinc 15 mg/1 1
INACTIVE INGREDIENTS: FRUCTOSE; STEARIC ACID; CROSCARMELLOSE SODIUM; MALTODEXTRIN; HYPROMELLOSES; SILICON DIOXIDE; CITRIC ACID MONOHYDRATE; TITANIUM DIOXIDE; POLYDEXTROSE; MAGNESIUM STEARATE; MALIC ACID; HYDROXYPROPYL CELLULOSE (TYPE H); TRIACETIN; STARCH, CORN; SUCROSE; ACACIA; POLYETHYLENE GLYCOLS; CALCIUM PHOSPHATE, DIBASIC, ANHYDROUS; FD&C BLUE NO. 1; FD&C BLUE NO. 2; SODIUM ASCORBATE; MEDIUM-CHAIN TRIGLYCERIDES; .ALPHA.-TOCOPHEROL, DL-

SELECT-OB®
Prenatal Supplement

Rx only

COMPOSITION

Each caplet contains:
Vitamin A | 1,700 IU
Vitamin C | 60 mg
Vitamin D | 400 IU
Vitamin E | 30 IU
Thiamine Mononitrate (Vitamin B1) | 1.6 mg
Riboflavin (Vitamin B2) | 1.8 mg
Niacin (as niacinamide) | 15 mg
Vitamin B6 (as pyridoxine hydrochloride) | 2.5 mg
Folic Acid | 1 mg
Vitamin B12 (as Cyanocobalamin) | 5 mcg
Elemental Iron (as polysaccharide iron complex) | 29 mg
Magnesium (as magnesium oxide) | 25 mg
Zinc (as zinc oxide) | 15 mg

Other Ingredients: Fructose, Stearic Acid, Mono and Diglycerides, Croscarmellose Sodium, Mixed Berry Flavor WONF, Gelatin (Porcine), Silicon Dioxide, Citric Acid, Magnesium Stearate, Modified Food Starch, Hydroxypropylmethyl Cellulose, Malic Acid, Sucrose, Corn Starch, Dicalcium Phosphate, Sodium Ascorbate, Medium Chain Triglycerides, Sorbic Acid, Tocopherol Concentrate, Sodium Benzoate, dl-Alpha-Tocopherol, Butylated Hydroxytoluene (BHT), Tricalcium Phosphate. Coating: Hydroxypropylmethyl Cellulose, Titanium Dioxide, Polydextrose, Hydroxypropyl Cellulose, Triacetin, Polyethylene Glycol, FD&C Blue #1/Aluminum Lake, FD&C Blue #2/Aluminum Lake. Contains Soy.

INDICATIONS AND USAGE

SELECT-OB® is indicated to provide vitamin, mineral supplementation prior to conception, throughout pregnancy, and during the postnatal period for the lactating and non-lactating mother.

CONTRAINDICATIONS

SELECT-OB® is contraindicated in patients with hypersensitivity to any of its components or color additives.

Folic acid is contraindicated in patients with untreated and uncomplicated pernicious anemia, and in those with anaphylactic sensitivity to folic acid. Iron therapy is contraindicated in patients with hemochromatosis and patients with iron storage disease or the potential for iron storage disease due to chronic hemolytic anemia (e.g., inherited anomalies of hemoglobin structure or synthesis and/or red cell enzyme deficiencies, etc.), pyridoxine responsive anemia, or cirrhosis of the liver.

Cyanocobalamin is contraindicated in patients with sensitivity to cobalt or to cyanocobalamin (vitamin B12).

WARNING

Accidental overdose of iron-containing products is a leading cause of fatal poisoning in children under 6. Keep this product out of the reach of children. In case of accidental overdose, call a doctor or a Poison Control Center immediately.

WARNINGS/PRECAUTIONS

SELECT-OB® should be used with caution in patients with known sensitivity or allergy to soy.

Vitamin D supplementation should be used with caution in those with hypercalcemia or conditions that may lead to hypercalcemia such as hyperparathyroidism and those who form calcium-containing kidney stones. High doses of vitamin D can lead to elevated levels of calcium that reside in the blood and soft tissues. Bone pain, high blood pressure, formation of kidney stones, renal failure, and increased risk of heart disease can occur. Prolonged use of iron salts may produce iron storage disease.

Folic acid, especially in doses above 0.1 mg daily, may obscure pernicious anemia, in that hematologic remission may occur while neurological manifestations remain progressive. The use of folic acid doses above 1 mg daily may precipitate or exacerbate the neurological damage of vitamin B12 deficiency. Consumption of more than 3 grams of omega-3 fatty acids per day from all sources may lead to excessive bleeding.

Supplemental intake of omega-3 fatty acids such as DHA exceeding 2 grams per day is not recommended. Avoid overdosage. Keep out of the reach of children.

PRECAUTIONS

Drug Interactions

High doses of folic acid may result in decreased serum levels of the anticonvulsant drugs. Vitamin D supplementation should not be given with large amounts of calcium in those with hypercalcemia or conditions that may lead to hypercalcemia such as hyperparathyroidism and those who form calcium-containing kidney stones.

Zinc can inhibit the absorption of certain antibiotics; take at least 2 hours apart to minimize interactions. Consult appropriate references for additional specific vitamin-drug interactions.

Information for Patients

Patients should be counseled to disclose all medical conditions, including use of all medications, vitamins and supplements, pregnancy, and breast-feeding.

Pediatric Use

Not for pediatric use.

ADVERSE REACTIONS

Adverse reactions have been reported with specific vitamins and minerals, but generally at doses substantially higher than those in SELECT-OB®.

DOSAGE AND ADMINISTRATION

Before, during and after pregnancy, one caplet daily, or as directed by a physician.

HOW SUPPLIED

SELECT-OB® is available as a light blue caplet debossed EV0077. Available in bottle of 90, (NDC 0642-0077-90).

STORAGE AND HANDLING

Store at room temperature, approximately 15°-30°C (59°-86°F), avoid excessive heat and moisture.

Rx only

Manufactured for:
EVERETT LABORATORIES, INC.
Chatham, NJ 07928
1-877-324-9349

U.S. Patent No. 7,560,123 / 8,101,587 / 8,197,855
Select-OB® is a trademark of
Everett Laboratories, Inc.

Rev. 03/13
6876

PRINCIPAL DISPLAY PANEL - 90 Caplet Bottle Label

NDC 0642-0077-90

Select-OB®
Prenatal Supplement

90 Caplets
Rx only